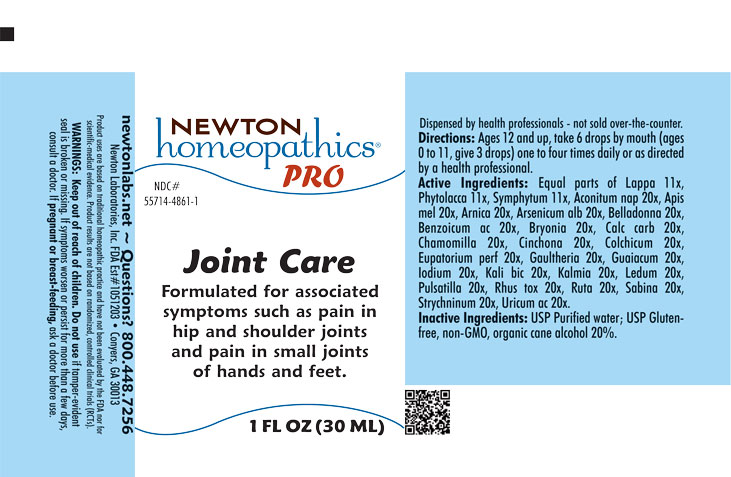 DRUG LABEL: Joint Care
NDC: 55714-4861 | Form: LIQUID
Manufacturer: Newton Laboratories, Inc.
Category: homeopathic | Type: HUMAN OTC DRUG LABEL
Date: 20250919

ACTIVE INGREDIENTS: MATRICARIA CHAMOMILLA 20 [hp_X]/1 mL; URIC ACID 20 [hp_X]/1 mL; ACONITUM NAPELLUS 20 [hp_X]/1 mL; APIS MELLIFERA 20 [hp_X]/1 mL; ARNICA MONTANA 20 [hp_X]/1 mL; ARSENIC TRIOXIDE 20 [hp_X]/1 mL; ATROPA BELLADONNA 20 [hp_X]/1 mL; BENZOIC ACID 20 [hp_X]/1 mL; BRYONIA ALBA ROOT 20 [hp_X]/1 mL; OYSTER SHELL CALCIUM CARBONATE, CRUDE 20 [hp_X]/1 mL; CINCHONA OFFICINALIS BARK 20 [hp_X]/1 mL; GUAIACUM OFFICINALE RESIN 20 [hp_X]/1 mL; COLCHICUM AUTUMNALE BULB 20 [hp_X]/1 mL; EUPATORIUM PERFOLIATUM FLOWERING TOP 20 [hp_X]/1 mL; GAULTHERIA PROCUMBENS TOP 20 [hp_X]/1 mL; IODINE 20 [hp_X]/1 mL; POTASSIUM DICHROMATE 20 [hp_X]/1 mL; KALMIA LATIFOLIA LEAF 20 [hp_X]/1 mL; RHODODENDRON TOMENTOSUM LEAFY TWIG 20 [hp_X]/1 mL; ANEMONE PULSATILLA 20 [hp_X]/1 mL; TOXICODENDRON PUBESCENS LEAF 20 [hp_X]/1 mL; RUTA GRAVEOLENS FLOWERING TOP 20 [hp_X]/1 mL; JUNIPERUS SABINA LEAFY TWIG 20 [hp_X]/1 mL; STRYCHNINE 20 [hp_X]/1 mL; ARCTIUM LAPPA ROOT 11 [hp_X]/1 mL; PHYTOLACCA AMERICANA ROOT 11 [hp_X]/1 mL; COMFREY ROOT 11 [hp_X]/1 mL
INACTIVE INGREDIENTS: ALCOHOL; WATER

Joint 4861L

INDICATIONS & USAGE SECTION

Formulated for associated symptoms such as pain in hip and shoulder joints and pain in small joints of hands and feet.

DOSAGE & ADMINISTRATION SECTION

Directions: Ages 12 and up, take 6 drops by mouth (ages 0 to 11, give 3 drops) one to four times daily or as directed by a health professional.

OTC - ACTIVE INGREDIENT SECTION

Equal parts of Lappa 11x, Phytolacca 11x, Symphytum 11x, Aconitum nap 20x, Apis mel 20x, Arnica 20x, Arsenicum alb 20x, Belladonna 20x, Benzoicum ac 20x, Bryonia 20x, Calc carb 20x, Chamomilla 20x, Cinchona 20x, Colchicum 20x, Eupatorium perf 20x, Gaultheria 20x, Guaiacum 20x, Iodium 20x, Kali bic 20x, Kalmia 20x, Ledum 20x, Pulsatilla 20x, Rhus tox 20x, Ruta 20x, Sabina 20x, Strychninum 20x, Uricum ac 20x.

OTC - PURPOSE SECTION

Formulated for associated symptoms such as pain in hip and shoulder joints and pain in small joints of hands and feet.

INACTIVE INGREDIENT SECTION

Inactive Ingredients: USP Purified Water; USP Gluten-free, non-GMO, organic cane alcohol 20%

QUESTIONS SECTION

newtonlabs.net - Questions? 800.448.7256

Newton Laboratories, Inc. FDA Est # 1051203 Conyers, GA 30013

WARNINGS SECTION

WARNINGS: Keep out of reach of children. Do not use if tamper-evident seal is broken or missing. If symptoms worsen or persist for more than a few days, consult a doctor. If pregnant or breast-feeding, ask a doctor before use.

OTC - PREGNANCY OR BREAST FEEDING SECTION

If pregnant or breast-feeding, ask a doctor before use.

OTC - KEEP OUT OF REACH OF CHILDREN SECTION

Keep out of reach of children.